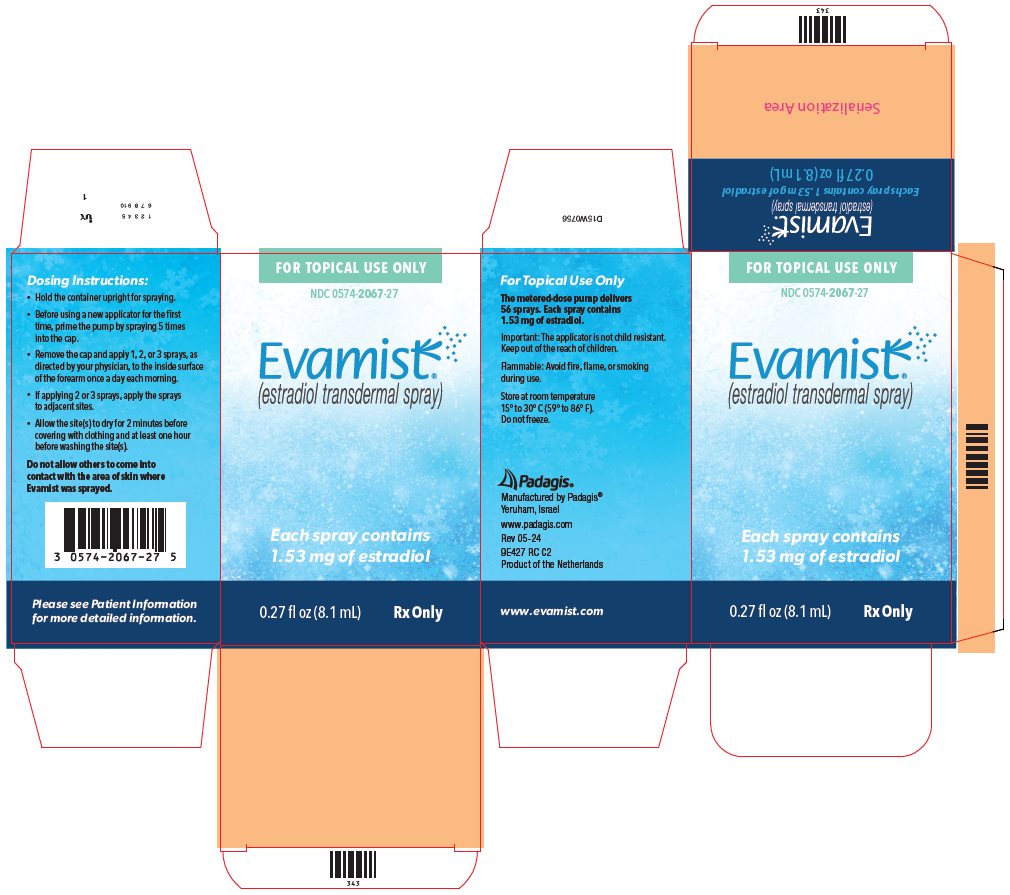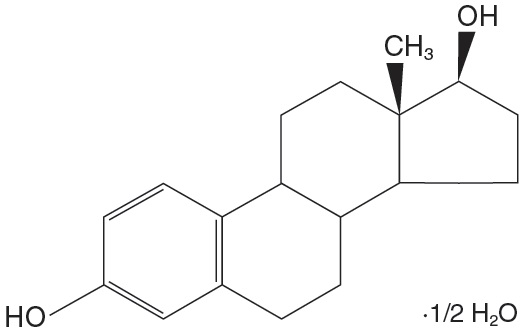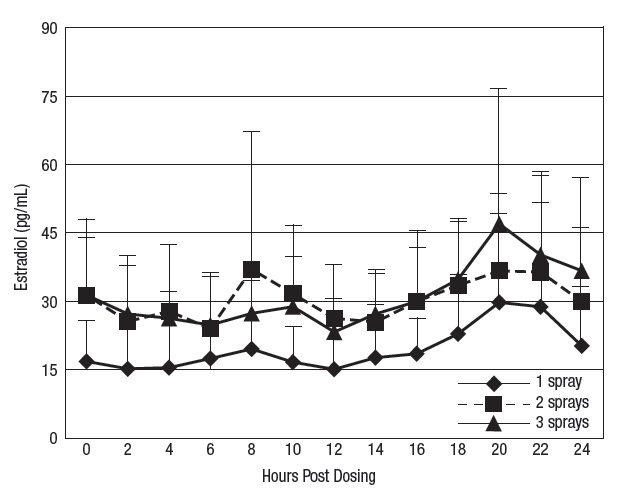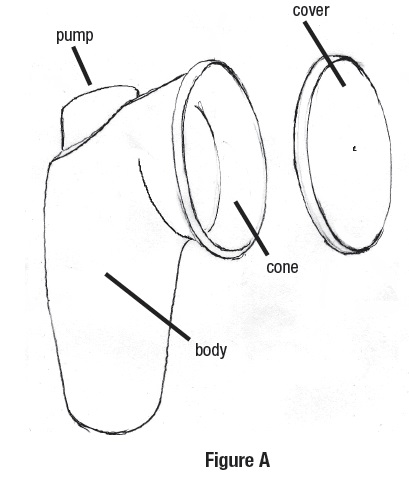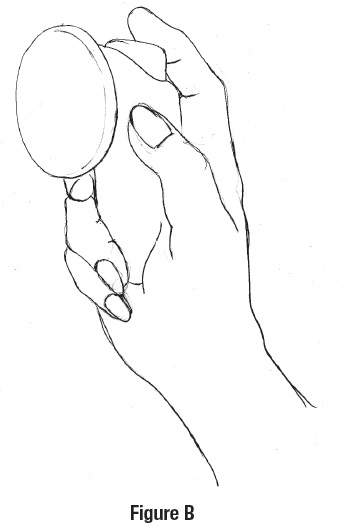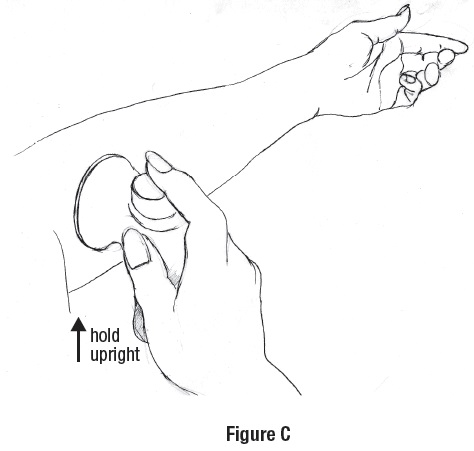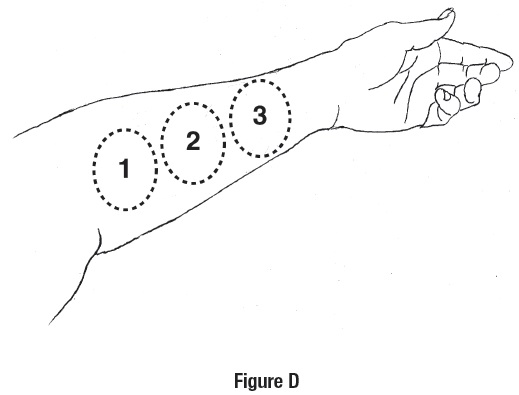 DRUG LABEL: Evamist
NDC: 0574-2067 | Form: SPRAY
Manufacturer: Padagis US LLC
Category: prescription | Type: HUMAN PRESCRIPTION DRUG LABEL
Date: 20241029

ACTIVE INGREDIENTS: ESTRADIOL 1.53 mg/1 1
INACTIVE INGREDIENTS: OCTISALATE; ALCOHOL

HIGHLIGHTS OF PRESCRIBING INFORMATION

These highlights do not include all the information needed to use EVAMIST safely and effectively. See full prescribing information for EVAMIST.
EVAMIST (estradiol transdermal spray)
Initial U.S. Approval: 1975

RECENT MAJOR CHANGES

Boxed Warning 08/2023

Warnings and Precautions, Malignant Neoplasms (5.2) 12/2023

BOXED WARNING

WARNING: ENDOMETRIAL CANCER, CARDIOVASCULAR DISORDERS, PROBABLE DEMENTIA, BREAST CANCER, and UNINTENTIONAL SECONDARY EXPOSURE TO ESTROGEN

See full prescribing information for complete boxed warning.

Estrogen-Alone Therapy

• There is an increased risk of endometrial cancer in a woman with a uterus who uses unopposed estrogens (5.2)

• The Women’s Health Initiative (WHI) estrogen-alone substudy reported increased risks of stroke and deep vein thrombosis (DVT) (5.1)

• The WHI Memory Study (WHIMS) estrogen-alone ancillary study of WHI reported an increased risk of probable dementia in postmenopausal women 65 years of age and older (5.3)

• Do not use estrogen-alone therapy for the prevention of cardiovascular disease or dementia (5.1, 5.3)

Estrogen Plus Progestin Therapy

• The WHI estrogen plus progestin substudy reported increased risks of pulmonary embolism (PE), DVT, stroke, and myocardial infarction (MI) (5.1)

• The WHI estrogen plus progestin substudy reported increased risks of invasive breast cancer (5.2)

• The WHIMS estrogen plus progestin ancillary study of WHI reported an increased risk of probable dementia in postmenopausal women 65 years of age and older (5.3)

• Do not use estrogen plus progestogen therapy for the prevention of cardiovascular disease or dementia (5.1, 5.3)

Unintentional Secondary Exposure

• Breast budding, breast masses, and gynecomastia have been reported in children following unintentional secondary exposure to Evamist (5.4)

1 INDICATIONS AND USAGE

Evamist is an estrogen indicated for the treatment of moderate to severe vasomotor symptoms due to menopause (1.1)

2 DOSAGE AND ADMINISTRATION

- Start therapy with one spray of Evamist once daily each morning to forearm (2.1)
- Dosage adjustment to two or three sprays of Evamist should be guided by the clinical response (2.1)

3 DOSAGE FORMS AND STRENGTHS

- Spray: One spray consists of 90 mcL which contains 1.53 mg estradiol (3)

4 CONTRAINDICATIONS

- Undiagnosed abnormal genital bleeding (4, 5.2)
- Breast cancer or a history of breast cancer (4, 5.2)
- Estrogen-dependent neoplasia (4, 5.2)
- Active DVT, PE, or history of these conditions (4, 5.1)
- Active arterial thromboembolic disease (for example, stroke and MI), or history of these conditions (4, 5.1)
- Known anaphylactic reaction, angioedema, or hypersensitivity to Evamist (4)
- Hepatic impairment or disease (4, 5.10)
- Protein C, protein S, or antithrombin deficiency, or other known thrombophilic disorders (4)

5 WARNINGS AND PRECAUTIONS

- Estrogens increase the risk of gallbladder disease (5.5)
- Discontinue estrogens if severe hypercalcemia, loss of vision, severe hypertriglyceridemia or cholestatic jaundice occurs (5.6, 5.7, 5.10, 5.11)
- Monitor thyroid function in women on thyroid hormone replacement therapy (5.12, 5.21)

6 ADVERSE REACTIONS

The most common adverse reactions (≥ 5 percent) with Evamist are: headache, breast tenderness and nipple pain, nausea, back pain, and nasopharyngitis. (6.1)

To report SUSPECTED ADVERSE REACTIONS, contact Padagis® at 1-866-634-9120 or FDA at 1-800-FDA-1088 or www.fda.gov/medwatch.

7 DRUG INTERACTIONS

- Inducers and inhibitors of CYP3A4 may affect estrogen drug metabolism and decrease or increase the estrogen plasma concentration. (7.1)

FULL PRESCRIBING INFORMATION

BOXED WARNING

WARNING: ENDOMETRIAL CANCER, CARDIOVASCULAR DISORDERS, PROBABLE DEMENTIA, BREAST CANCER, and UNINTENTIONAL SECONDARY EXPOSURE TO ESTROGEN

Estrogen-Alone Therapy

Endometrial Cancer

There is an increased risk of endometrial cancer in a woman with a uterus who uses unopposed estrogens. Adding a progestogen to estrogen therapy has been shown to reduce the risk of endometrial hyperplasia, which may be a precursor to endometrial cancer. Perform adequate diagnostic measures, including directed and random endometrial sampling when indicated, to rule out malignancy in all cases of undiagnosed persistent or recurring abnormal genital bleeding [see Warnings and Precautions (5.2)].

Cardiovascular Disorders and Probable Dementia

The Women’s Health Initiative (WHI) estrogen-alone substudy reported increased risks of stroke and deep vein thrombosis (DVT) in postmenopausal women (50 to 79 years of age) during 7.1 years of treatment with daily oral conjugated estrogens (CE) [0.625 mg]-alone, relative to placebo [see Warnings and Precautions (5.1), and Clinical Studies (14.2)].

The WHI Memory Study (WHIMS) estrogen-alone ancillary study of WHI reported an increased risk of developing probable dementia in postmenopausal women 65 years of age and older during 5.2 years of treatment with daily CE (0.625 mg)-alone, relative to placebo. It is unknown whether this finding applies to younger postmenopausal women [see Warnings and Precautions (5.3), Use in Specific Populations (8.5), and Clinical Studies (14.3)].

Do not use estrogen-alone therapy for the prevention of cardiovascular disease or dementia [see Warnings and Precautions (5.1, 5.3), and Clinical Studies (14.2, 14.3)].

Only daily oral 0.625 mg CE was studied in the estrogen-alone substudy of the WHI. Therefore, the relevance of the WHI findings regarding adverse cardiovascular events and dementia to lower CE doses, other routes of administration, or other estrogen-alone products is not known. Without such data, it is not possible to definitively exclude these risks or determine the extent of these risks for other products. Discuss with your patient the benefits and risks of estrogen-alone therapy, taking into account her individual risk profile.

Prescribe estrogens with or without progestogens at the lowest effective doses and for the shortest duration consistent with treatment goals and risks for the individual woman.

Estrogen Plus Progestin Therapy

Cardiovascular Disorders and Probable Dementia

The WHI estrogen plus progestin substudy reported increased risks of pulmonary embolism (PE), DVT, stroke and myocardial infarction (MI) in postmenopausal women (50 to 79 years of age) during 5.6 years of treatment with daily oral CE (0.625 mg) combined with medroxyprogesterone acetate (MPA) [2.5 mg], relative to placebo [see Warnings and Precautions (5.1), and Clinical Studies (14.2)].

The WHIMS estrogen plus progestin ancillary study of WHI reported an increased risk of developing probable dementia in postmenopausal women 65 years of age and older during 4 years of treatment with daily CE (0.625mg) combined with MPA (2.5 mg), relative to placebo. It is unknown whether this finding applies to younger postmenopausal women [see Warnings and Precautions (5.3), Use in Specific Populations (8.5), and Clinical Studies (14.3)].

Do not use estrogen plus progestogen therapy for the prevention of cardiovascular disease or dementia [see Warning and Precautions (5.1, 5.3), and Clinical Studies (14.2)].

Breast Cancer

The WHI estrogen plus progestin substudy demonstrated an increased risk of invasive breast cancer [see Warnings and Precautions (5.2), and Clinical Studies (14.2)].

Only daily oral 0.625 mg CE and 2.5 mg MPA were studied in the estrogen plus progestin substudy of the WHI. Therefore, the relevance of the WHI findings regarding adverse cardiovascular events, dementia and breast cancer to lower CE plus other MPA doses, other routes of administration, or other estrogen plus progestogen products is not known. Without such data, it is not possible to definitively exclude these risks or determine the extent of these risks for other products. Discuss with your patient the benefits and risks of estrogen plus progestogen therapy, taking into account her individual risk profile.

Prescribe estrogens with or without progestogens at the lowest effective doses and for the shortest duration consistent with treatment goals and risks for the individual woman.

Unintentional Secondary Exposure

Breast budding and breast masses in prepubertal females and gynecomastia and breast masses in prepubertal males have been reported following unintentional secondary exposure to Evamist by women using this product. In most cases, the condition resolved with removal of Evamist exposure. Women should ensure that children do not come into contact with the site(s) where Evamist is applied. Healthcare providers should advise patients to strictly adhere to recommended instructions for use [see Warnings and Precautions (5.4)].

2 DOSAGE AND ADMINISTRATION

Generally, when estrogen is prescribed for a postmenopausal woman with a uterus, consider addition of a progestogen to reduce the risk of endometrial cancer. Generally, a woman without a uterus does not need to use a progestogen in addition to her estrogen therapy. In some cases, however, hysterectomized women who have a history of endometriosis may need a progestogen [see Warnings and Precautions (5.2, 5.15)].

Use estrogen-alone, or in combination with a progestogen, at the lowest effective dose and for the shortest duration consistent with treatment goals and risks for the individual woman. Re-evaluate postmenopausal women periodically as clinically appropriate to determine whether treatment is still necessary.

2.1 Treatment of Moderate to Severe Vasomotor Symptoms due to Menopause

Start Evamist therapy with one spray of Evamist per day. Make dosage adjustment based on the clinical response.

Prime the Evamist container by spraying 5 sprays with the cover on before applying the first dose from a new applicator. Hold the container upright and vertical for spraying.

Apply one, two or three sprays each morning to adjacent, non-overlapping areas on the inner surface of the forearm, starting near the elbow. Allow the sprays to dry for approximately 2 minutes before covering the site with clothing. Do not wash the application site for at least one hour. Application of Evamist to other skin surfaces has not been adequately studied. Evamist should not be applied to skin surfaces other than the forearm.

Strict adherence to the following precautions is advised in order to minimize the potential for secondary exposure to estradiol from Evamist-treated skin. Cover the Evamist application site with clothing if another person may come into contact with that area of skin after the spray dries. Additional precautions to minimize unintentional secondary exposure are outlined in Patient Counseling Information [see Patient Counseling Information] and in the Patient Information Leaflet at the end of the prescribing information.

3 DOSAGE FORMS AND STRENGTHS

Evamist is an estradiol transdermal spray. One spray consists of 90 mcL that contains 1.53 mg of estradiol.

4 CONTRAINDICATIONS

Evamist is contraindicated in women with any of the following conditions:

- Undiagnosed abnormal genital bleeding [see Warnings and Precautions (5.2)].
- Breast cancer or a history of breast cancer [see Warnings and Precautions (5.2)].
- Estrogen-dependent neoplasia [see Warnings and Precautions (5.2)].
- Active DVT, PE, or history of these conditions [see Warnings and Precautions (5.1)].
- Active arterial thromboembolic disease (for example, stroke or MI), or a history of these conditions [see Warnings and Precautions (5.1)].
- Known anaphylactic reaction, angioedema, or hypersensitivity to Evamist.
- Hepatic impairment or disease.
- Protein C, protein S, or antithrombin deficiency, or other known thrombophilic disorders.

5 WARNINGS AND PRECAUTIONS

5.1 Cardiovascular Disorders

Increased risks of stroke and DVT are reported with estrogen-alone therapy. Increased risks of PE, DVT, stroke, and MI are reported with estrogen plus progestin therapy. Should any of these occur or be suspected, estrogen with or without progestin therapy should be discontinued.

Immediately discontinue estrogen with or without progestogen therapy if any of these occur or are suspected.

Manage appropriately any risk factors for arterial vascular disease (for example, hypertension, diabetes mellitus, tobacco use, hypercholesterolemia, and obesity) and/or venous thromboembolism (VTE) (for example, personal history or family history of VTE, obesity, and systemic lupus erythematosus).

Stroke

The WHI estrogen-alone substudy reported a statistically significant increased risk of stroke in women 50 to 79 years of age receiving daily CE (0.625 mg)-alone compared to women in the same age group receiving placebo (45 versus 33 strokes per 10,000 women-years, respectively). The increase in risk was demonstrated in year 1 and persisted [see Clinical Studies (14.2)]. Immediately discontinue estrogen-alone therapy if a stroke occurs or is suspected.

Subgroup analyses of women 50 to 59 years of age suggest no increased risk of stroke for those women receiving CE (0.625 mg)-alone versus those receiving placebo (18 versus 21 per 10,000 women-years).^1

The WHI estrogen plus progestin substudy reported a statistically significant increased risk of stroke in women 50 to 79 years of age receiving daily CE (0.625 mg) plus MPA (2.5 mg) compared to women in the same age group receiving placebo (33 versus 25 strokes per 10,000 women-years, respectively) [see Clinical Studies (14.2)]. The increase in risk was demonstrated after the first year and persisted.^1 Immediately discontinue estrogen plus progestogen therapy if a stroke occurs or is suspected.

Coronary Heart Disease

The WHI estrogen-alone substudy reported no overall effect on coronary heart disease (CHD) events (defined as non-fatal MI, silent MI, or CHD death) in women receiving estrogen-alone compared to placebo^2 [see Clinical Studies (14.2)].

Subgroup analysis of women 50 to 59 years of age, who were less than 10 years since menopause, suggest a reduction (not statistically significant) of CHD events in those women receiving daily CE (0.635 mg)-alone compared to placebo) (8 versus 16 per 10,000 women-years)^1.

The WHI estrogen plus progestin substudy reported an increased risk (not statistically significant) of CHD events in women receiving daily CE (0.625 mg) plus MPA (2.5 mg) compared to women receiving placebo (41 versus 34 per 10,000 women-years)^1. An increase in relative risk was demonstrated in year 1, and a trend toward decreasing relative risk was reported in years 2 through 5 [see Clinical Studies (14.2)].

In postmenopausal women with documented heart disease (n = 2,763), average 66.7 years of age, in a controlled clinical trial of secondary prevention of cardiovascular disease (Heart and Estrogen/Progestin Replacement Study; (HERS), treatment with daily CE (0.625 mg) plus MPA (2.5 mg) demonstrated no cardiovascular benefit. During an average follow-up of 4.1 years, treatment with CE plus MPA did not reduce the overall rate of CHD events in postmenopausal women with established CHD. There were more CHD events in the CE plus MPA-treated group than in the placebo group in year 1, but not during the subsequent years. Two thousand, three hundred and twenty-one (2,321) women from the original HERS trial agreed to participate in an open label extension of the original HERS, HERS II. Average follow-up in HERS II was an additional 2.7 years, for a total of 6.8 years overall. Rates of CHD events were comparable among women in the CE plus MPA group and the placebo group in HERS, HERS II, and overall.

Venous Thromboembolism

In the WHI estrogen-alone substudy, the risk of VTE (DVT and PE) was increased for women receiving daily CE (0.625 mg)-alone compared to placebo (30 versus 22 per 10,000 women-years), although only the increased risk of DVT reached statistical significance (23 versus 15 per 10,000 women-years). The increase in VTE risk was demonstrated during the first two years^3 [see Clinical Studies (14.2)]. Immediately discontinue estrogen-alone therapy if a VTE occurs or is suspected.

The WHI estrogen plus progestin substudy reported a statistically significant 2-fold greater rate of VTE in women receiving daily CE (0.625 mg) plus MPA (2.5 mg) compared to women receiving placebo (35 versus 17 per 10,000 women-years). Statistically significant increases in risk for both DVT (26 versus 13 per 10,000 women-years) and PE (18 versus 8 per 10,000 women-years) were also demonstrated. The increase in VTE risk was observed during the first year and persisted^4 [see Clinical Studies (14.2)]. Immediately discontinue estrogen plus progestogen therapy if a VTE occurs or is suspected.

If feasible, discontinue estrogens at least 4 to 6 weeks before surgery of the type associated with an increased risk of thromboembolism, or during periods of prolonged immobilization.

5.2 Malignant Neoplasms

Endometrial Cancer

An increased risk of endometrial cancer has been reported with the use of unopposed estrogen therapy in women with a uterus. The reported endometrial cancer risk among unopposed estrogen users is about 2- to 12- times greater than in nonusers, and appears dependent on duration of treatment and on estrogen dose. Most studies show no significant increased risk associated with use of estrogens for less than 1 year. The greatest risk appears associated with prolonged use, with an increased risk of 15- to 24-fold for 5 to 10 years or more and this risk has been shown to persist for at least 8 to 15 years after estrogen therapy is discontinued.

Clinical surveillance of all women using estrogen-alone or estrogen plus progestogen therapy is important. Perform adequate diagnostic measures, including directed or random endometrial sampling when indicated, to rule out malignancy in all cases of undiagnosed persistent or recurring abnormal genital bleeding with unknown etiology. There is no evidence that the use of natural estrogens results in a different endometrial risk profile than synthetic estrogens of equivalent estrogen dose. Adding a progestogen to postmenopausal estrogen therapy has been shown to reduce the risk of endometrial hyperplasia, which may be a precursor to endometrial cancer.

Breast Cancer

The WHI substudy of daily CE (0.625 mg)-alone provided information about breast cancer in estrogen-alone users. In the WHI estrogen alone substudy, after an average follow-up of 7.1 years, daily CE-alone was not associated with an increased risk of invasive breast cancer (relative risk [RR] 0.80) compared to placebo^5 [see Clinical Studies (14.2)].

After a mean follow-up of 5.6 years, the WHI substudy of daily CE (0.625 mg) plus MPA (2.5 mg) reported an increased risk of invasive breast cancer in women who took daily CE plus MPA compared to placebo. In this substudy, prior use of estrogen-alone or estrogen plus progestin therapy was reported by 26 percent of the women. The relative risk of invasive breast cancer was 1.24 and the absolute risk was 41 versus 33 cases per 10,000 women-years, for CE plus MPA compared with placebo [see Clinical Studies (14.2)]. Among women who reported prior use of hormone therapy, the relative risk of invasive breast cancer was 1.86, and the absolute risk was 46 versus 25 cases per 10,000 women-years, for CE plus MPA compared with placebo. Among women who reported no prior use of hormone therapy, the relative risk of invasive breast cancer was 1.09, and the absolute risk was 40 versus 36 cases per 10,000 women-years for CE plus MPA compared with placebo. In the same substudy, invasive breast cancers were larger, were more likely to be node positive, and were diagnosed at a more advanced stage in the CE (0.625 mg) plus MPA (2.5 mg) group compared with the placebo group. Metastatic disease was rare, with no apparent difference between the two groups. Other prognostic factors, such as histologic subtype, grade and hormone receptor status did not differ between the groups^6 [see Clinical Studies (14.2)].

Consistent with the WHI clinical trials, observational studies have also reported an increased risk of breast cancer with estrogen plus progestin therapy, and a smaller increase in the risk for breast cancer with estrogen-alone therapy, after several years of use. One large meta-analysis of prospective cohort studies reported increased risks that were dependent upon duration of use and could last up to >10 years after discontinuation of estrogen plus progestin therapy and estrogen-alone therapy. Extension of the WHI trials also demonstrated increased breast cancer risk associated with estrogen plus progestin therapy. Observational studies also suggest that the risk of breast cancer was greater, and became apparent earlier, with estrogen plus progestin therapy as compared to estrogen-alone therapy. These studies have not generally found significant variation in the risk of breast cancer among different estrogen plus progestin combinations, doses, or routes of administration.

The use of estrogen-alone and estrogen plus progestin has been reported to result in an increase in abnormal mammograms requiring further evaluation.

All women should receive yearly breast examinations by a healthcare provider and perform monthly breast self-examinations. In addition, mammography examinations should be scheduled based on patient age, risk factors, and prior mammogram results.

Ovarian Cancer

The CE plus MPA substudy of WHI reported that estrogen plus progestin increased the risk of ovarian cancer. After an average follow-up of 5.6 years, the relative risk for ovarian cancer for CE plus MPA versus placebo was 1.58 (95 percent CI, 0.77-3.24) but it was not statistically significant. The absolute risk for CE plus MPA versus placebo was 4 versus 3 cases per 10,000 women-years.^7

A meta-analysis of 17 prospective and 35 retrospective epidemiology studies found that women who used hormonal therapy for menopausal symptoms had an increased risk for ovarian cancer. The primary analysis, using case-control comparisons, included 12,110 cancer cases from the 17 prospective studies. The relative risks associated with current use of hormonal therapy was 1.41 (95% CI, 1.32 to 1.50); there was no difference in the risk estimates by duration of the exposure (less than 5 years [median of 3 years] vs. greater than 5 years [median of 10 years] of use before the cancer diagnosis). The relative risk associated with combined current and recent use (discontinued use within 5 years before cancer diagnosis) was 1.37 (95% CI 1.27-1.48), and the elevated risk was significant for both estrogen-alone and estrogen plus progestin products. The exact duration of hormone therapy use associated with an increased risk of ovarian cancer, however, is unknown.

5.3 Probable Dementia

In the WHI Memory Study (WHIMS) estrogen-alone ancillary study, a population of 2,947 hysterectomized women 65 to 79 years of age was randomized to daily CE (0.625 mg)-alone or placebo. After an average follow-up of 5.2 years, 28 women in the estrogen-alone group and 19 women in the placebo group were diagnosed with probable dementia. The relative risk of probable dementia for CE-alone versus placebo was 1.49 (95 percent CI, 0.83-2.66). The absolute risk of probable dementia for CE-alone versus placebo was 37 versus 25 cases per 10,000 women-years^8 [see Use in Specific Populations (8.5) and Clinical Studies (14.3)].

In the WHIMS estrogen plus progestin ancillary study, a population of 4,532 postmenopausal women 65 to 79 years of age was randomized to daily CE (0.625 mg) plus MPA (2.5 mg) or placebo. After an average follow-up of 4 years, 40 women in the CE plus MPA group and 21 women in the placebo group were diagnosed with probable dementia. The relative risk of probable dementia for CE plus MPA versus placebo was 2.05 (95 percent CI, 1.21-3.48). The absolute risk of probable dementia for CE plus MPA versus placebo was 45 versus 22 cases per 10,000 women-years^8 [see Use in Specific Populations (8.5) and Clinical Studies (14.3)].

When data from the two populations in the WHIMS estrogen-alone and estrogen plus progestin ancillary studies were pooled as planned in the WHIMS protocol, the reported overall relative risk for probable dementia was 1.76 (95 percent CI, 1.19-2.60). Since both ancillary studies were conducted in women 65 to 79 years of age, it is unknown whether these findings apply to younger postmenopausal women^8 [see Use in Specific Populations (8.5) and Clinical Studies (14.3)].

5.4 Unintentional Secondary Exposure to Estrogen

Postmarketing reports of breast budding and breast masses in prepubertal females and gynecomastia and breast masses in prepubertal males following unintentional secondary exposure to Evamist are reported. In most cases, the condition resolved with removal of Evamist exposure.

Unexpected changes in breast tissue or other signs of abnormal sexual development in prepubertal children as well as the possibility of unintentional secondary exposure to Evamist should be brought to the attention of a physician. The physician should identify the cause of abnormal sexual development in the child. If unexpected breast development or changes are determined to be the result of unintentional exposure to Evamist, the physician should counsel the woman on the appropriate use and handling of Evamist when around children. Women should cover the Evamist application site with clothing if another person may come into contact with the site. Discontinue Evamist if conditions for safe use cannot be met [see Patient Counseling Information (17)].

5.5 Gallbladder Disease

A 2- to 4-fold increase in the risk of gallbladder disease requiring surgery in postmenopausal women receiving estrogens has been reported.

5.6 Hypercalcemia

Estrogen administration may lead to severe hypercalcemia in women with breast cancer and bone metastases. Discontinue estrogens, including Evamist if hypercalcemia occurs, and take appropriate measures to reduce the serum calcium level.

5.7 Visual Abnormalities

Retinal vascular thrombosis has been reported in women receiving estrogens. Discontinue Evamist pending examination if there is sudden partial or complete loss of vision, or a sudden onset of proptosis, diplopia, or migraine. Permanently discontinue estrogens, including Evamist, if examination reveals papilledema or retinal vascular lesions.

5.8 Addition of a Progestogen When a Woman Has Not Had a Hysterectomy

Studies of the addition of a progestogen for 10 or more days of a cycle of estrogen administration, or daily with estrogen in a continuous regimen, have reported a lowered incidence of endometrial hyperplasia than would be induced by estrogen treatment alone. Endometrial hyperplasia may be a precursor to endometrial cancer.

There are, however, possible risks that may be associated with the use of progestogens with estrogens compared to estrogen-alone regimens. These include an increased risk of breast cancer.

5.9 Elevated Blood Pressure

In a small number of case reports, substantial increases in blood pressure have been attributed to idiosyncratic reactions to estrogens. In a large, randomized, placebo-controlled clinical trial, a generalized effect of estrogens on blood pressure was not seen.

5.10 Exacerbation of Hypertriglyceridemia

In women with preexisting hypertriglyceridemia, estrogen therapy may be associated with elevations of plasma triglycerides leading to pancreatitis. Discontinue Evamist if pancreatitis occurs.

5.11 Hepatic Impairment and/or Past History of Cholestatic Jaundice

Estrogens may be poorly metabolized in women with hepatic impairment. Exercise caution in any women with a history of cholestatic jaundice associated with past estrogen use or with pregnancy. In the case of recurrence of cholestatic jaundice, discontinue Evamist.

5.12 Exacerbation of Hypothyroidism

Estrogen administration leads to increased thyroid-binding globulin (TBG) levels. Women with normal thyroid function can compensate for the increased TBG by making more thyroid hormone, thus maintaining free T4 and T3 serum concentrations in the normal range. Women dependent on thyroid hormone replacement therapy who are also receiving estrogens may require increased doses of their thyroid replacement therapy. Monitor thyroid function in these women during treatment with Evamist to maintain their free thyroid hormone levels in an acceptable range.

5.13 Fluid Retention

Estrogens may cause some degree of fluid retention. Monitor any woman with a condition(s) that might predispose her to fluid retention, such as a cardiac or renal impairment. Discontinue estrogen-alone therapy, including Evamist, with evidence of medically concerning fluid retention.

5.14 Hypocalcemia

Estrogen-induced hypocalcemia may occur in women with hypoparathyroidism. Consider whether the benefits of estrogen therapy, including Evamist, outweigh the risks in such women.

5.15 Exacerbation of Endometriosis

A few cases of malignant transformation of residual endometrial implants have been reported in women treated post-hysterectomy with estrogen-alone therapy. Consider the addition of progestogen therapy for women known to have residual endometriosis post-hysterectomy.

5.16 Hereditary Angioedema

Exogenous estrogens may exacerbate symptoms of angioedema in women with hereditary angioedema. Consider whether the benefits of estrogen therapy, including Evamist, outweigh the risks in such women.

5.17 Exacerbation of Other Conditions

Estrogen therapy, including Evamist, may cause an exacerbation of asthma, diabetes mellitus, epilepsy, migraine, porphyria, systemic lupus erythematosus and hepatic hemangiomas. Consider whether the benefits of estrogen therapy outweigh the risks in women with such conditions.

5.18 Alcohol-Based Products are Flammable

Avoid fire, flame or smoking until the spray has dried.

5.19 Application of Sunscreen

When sunscreen is applied approximately one hour after application of Evamist, estradiol absorption was decreased by 11 percent. When sunscreen is applied approximately one hour before the application of Evamist, no significant change in estradiol absorption was observed.

5.20 Laboratory Tests

Serum follicle stimulating hormone (FSH) and estradiol levels have not been shown to be useful in the management of postmenopausal women with moderate to severe vasomotor symptoms.

5.21 Drug and Laboratory Test Interactions

- Accelerated prothrombin time, partial thromboplastin time, and platelet aggregation time; increased platelet count; increased factors II, VII antigen, VIII antigen, VIII coagulant activity, IX, X, XII, VII-X complex, II-VII-X complex, and beta-thromboglobulin; decreased levels of antifactor Xa and antithrombin III, decreased antithrombin III activity; increased levels of fibrinogen and fibrinogen activity; increased plasminogen antigen and activity.
- Increased TBG levels leading to increased circulating total thyroid hormone levels, as measured by protein-bound iodine (PBI), T4 levels (by column or by radioimmunoassay) or T3 levels by radioimmunoassay. T3 resin uptake is decreased, reflecting the elevated TBG. Free T4 and free T3 concentrations are unaltered. Women on thyroid replacement therapy may require higher doses of thyroid hormone.
- Other binding proteins may be elevated in serum, for example, corticosteroid binding globulin (CBG), sex hormone binding globulin (SHBG), leading to increased total circulating corticosteroids and sex steroids, respectively. Free hormone concentrations, such as testosterone and estradiol, may be decreased. Other plasma proteins may be increased (angiotensinogen/rennin substrate, alpha-1-antitrypsin, ceruloplasmin).
- Increased plasma high-density lipoprotein (HDL) and HDL2 cholesterol subfraction concentrations, reduced low-density lipoprotein (LDL) cholesterol concentration, increased triglyceride levels.
- Impaired glucose tolerance.

6 ADVERSE REACTIONS

The following serious adverse reactions are discussed elsewhere in the labeling:

- Cardiovascular Disorders [see Boxed Warning, Warnings and Precautions (5.1)]
- Malignant Neoplasms [see Boxed Warning, Warnings and Precautions (5.2)]

6.1 Clinical Trials Experience

Because clinical trials are conducted under widely varying conditions, adverse reaction rates observed in the clinical trials of a drug cannot be directly compared to rates in the clinical trials of another drug and may not reflect the rates observed in clinical practice.

In a 12-week, randomized, placebo-controlled trial of Evamist in 454 women, 80 to 90 percent of women randomized to active drug received at least 70 days of therapy and 75 to 85 percent randomized to placebo received at least 70 days of therapy.

The adverse reactions that occurred in at least 5 percent of women in any treatment group are shown in Table 1.

Table 1. Frequency of Adverse Reactions (≥5%) in Any Treatment Group in a Controlled Study of Evamist

 | Frequency n (%)
System Organ Class; Preferred Term | 1 Spray |  | 2 Sprays |  | 3 Sprays
System Organ Class; Preferred Term | Placebo; (N = 77) | Evamist; (N = 76) | Placebo; (N = 76) | Evamist; (N = 74) | Placebo; (N = 75) | Evamist; (N = 76)
Reproductive System and Breast Disorders
Breast tenderness | 0 (0) | 4 (5) | 4 (5) | 5 (7) | 0 (0) | 4 (5)
Nipple pain | 0 (0) | 2 (3) | 0 (0) | 5 (7) | 0 (0) | 1 (1)
Gastrointestinal Disorders
Nausea | 5 (7) | 1 (1) | 1 (1) | 2 (3) | 4 (5) | 2 (3)
Infections and Infestations
Nasopharyngitis | 1 (1) | 4 (5) | 2 (3) | 3 (4) | 1 (1) | 1 (1)
Musculoskeletal and Connective Tissue Disorders
Back pain | 1 (1) | 2 (3) | 2 (3) | 4 (5) | 1 (1) | 2 (3)
Arthralgia | 1 (1) | 1 (1) | 4 (5) | 1 (1) | 0 (0) | 3 (4)
Nervous system
Headache | 4 (5) | 7 (9) | 5 (7) | 9 (12) | 7 (9) | 8 (11)

Application site reactions were reported in 3 out of 226 (1.3%) women treated with Evamist.

6.2 Postmarketing Experience

The following additional adverse reactions have been identified during post-approval use of Evamist. Because these reactions are reported voluntarily from a population of uncertain size, it is not always possible to reliably estimate their frequency or establish a causal relationship to drug exposure.

Breasts: Breast swelling, breast mass, breast enlargement

Cardiovascular: Heart rate increased

Central nervous system: Dizziness, dysgeusia, paresthesia, lethargy, hypoesthesia

Eyes: Eye irritation, ocular hyperemia

Gastrointestinal: Abdominal pain, diarrhea, constipation, abdominal distension, dry mouth, decreased appetite

Genitourinary system: Vaginal bleeding

Musculoskeletal: Muscle spasms, arthritis

Psychiatric: Insomnia, mood swings, anxiety, irritability, mood altered, depression

Respiratory tract: Cough, dyspnea, dry throat

Skin: Nipple and areola discoloration, usually on the same side of the body as the inner forearm on which Evamist is applied, rash, pruritus, alopecia, urticaria, dry skin, skin discoloration, chloasma

Miscellaneous: Weight increased, malaise, fatigue, asthenia

7 DRUG INTERACTIONS

In vitro and in vivo studies have shown that estrogens are metabolized partially by cytochrome P450 3A4 (CYP3A4). Therefore, inducers or inhibitors of CYP3A4 may affect estrogen drug metabolism. Inducers of CYP3A4 such as St. John's wort (Hypericum perforatum) preparations, phenobarbital, carbamazepine, and rifampin may reduce plasma concentrations of estrogens, possibly resulting in a decrease in therapeutic effects and/or changes in the uterine bleeding profile. Inhibitors of CYP3A4 such as erythromycin, clarithromycin, ketoconazole, itraconazole, ritonavir and grapefruit juice may increase plasma concentrations of estrogens and may result in adverse reactions.

8 USE IN SPECIFIC POPULATIONS

8.1 Pregnancy

Risk Summary

Evamist is not indicated for use in pregnancy. There are no data with the use of Evamist in pregnant women; however, epidemiologic studies and meta-analyses have not found an increased risk of genital or nongenital birth defects (including cardiac anomalies and limb-reduction defects) following exposure to combined hormonal contraceptives (estrogens and progestins) before conception or during early pregnancy.

In the U.S. general population, the estimated background risk of major birth defects and miscarriage in clinically recognized pregnancies is 2% to 4% and 15% to 20%, respectively.

8.2 Lactation

Risk Summary

Estrogens are present in human milk and can reduce milk production in breast-feeding females. This reduction can occur at any time but is less likely to occur once breast-feeding is well-established. The developmental and health benefits of breastfeeding should be considered along with the mother’s clinical need for Evamist and any potential adverse effects on the breastfed child from Evamist or from the underlying maternal condition.

8.4 Pediatric Use

Evamist is not indicated for use in pediatric patients. Clinical studies have not been conducted in the pediatric population.

8.5 Geriatric Use

There have not been sufficient numbers of geriatric women involved in clinical studies utilizing Evamist to determine whether those over 65 years of age differ from younger subjects in their response to Evamist.

The Women’s Health Initiative Studies

In the WHI estrogen-alone substudy (daily CE [0.625 mg]-alone versus placebo), there was a higher relative risk of stroke in women greater than 65 years of age [see Clinical Studies (14.2)].

In the WHI estrogen plus progestin substudy (daily CE [0.625 mg] plus MPA [2.5 mg] versus placebo), there was a higher relative risk of nonfatal stroke and invasive breast cancer in women greater than 65 years of age [see Clinical Studies (14.2)].

The Women’s Health Initiative Memory Study

In the WHIMS ancillary studies of postmenopausal women 65 to 79 years of age, there was an increased risk of developing probable dementia in women receiving estrogen-alone or estrogen plus progestin when compared to placebo [see Warnings and Precautions (5.3), and Clinical Studies (14.3)].

Since both ancillary studies were conducted in women 65 to 79 years of age, it is unknown whether these findings apply to younger postmenopausal women^8 [see Warnings and Precautions (5.3), and Clinical Studies (14.3)].

10 OVERDOSAGE

Overdosage of estrogen may cause nausea and vomiting, breast tenderness, abdominal pain, drowsiness and fatigue, and withdrawal bleeding may occur in women. Treatment of overdose consists of discontinuation of Evamist therapy with institution of appropriate symptomatic care.

11 DESCRIPTION

Evamist (estradiol transdermal spray) is designed to deliver estradiol to the blood circulation following topical application to the skin of a rapidly drying solution from a metered-dose pump.

Evamist is a homogeneous solution of 1.7% estradiol USP (active ingredient) in alcohol USP and octisalate USP formulated to provide sustained release of the active ingredient into the systemic circulation.

Estradiol USP is a white crystalline powder, chemically described as estra-1,3,5(10)-triene- 3,17β-diol. It has an empirical formula of C18H24O2•1/2 H2O and molecular weight of 281.4. The structural formula is:

Each metered-dose pump contains 8.1 mL and is designed to deliver 56 sprays of 90 mcL each after priming. One spray of Evamist contains 1.53 mg estradiol. The metered-dose pump should be held upright and vertical for spraying. Before a new applicator is used for the first time, the pump should be primed by spraying 5 times with the cover on.

One, two or three sprays are applied daily each morning to adjacent non-overlapping 20 cm^2 areas on the inner surface of the arm between the elbow and the wrist and allowed to dry.

12 CLINICAL PHARMACOLOGY

12.1 Mechanism of Action

Endogenous estrogens are largely responsible for the development and maintenance of the female reproductive system and secondary sexual characteristics. Although circulating estrogens exist in a dynamic equilibrium of metabolic interconversions, estradiol is the principal intracellular human estrogen and is substantially more potent than its metabolites, estrone and estriol, at the receptor level.

The primary source of estrogen in normally cycling adult women is the ovarian follicle, which secretes 70 to 500 mcg of estradiol daily, depending on the phase of the menstrual cycle. After menopause, most endogenous estrogen is produced by conversion of androstenedione, secreted by the adrenal cortex, to estrone in the peripheral tissues. Thus, estrone and the sulfate conjugated form, estrone sulfate, are the most abundant circulating estrogens in postmenopausal women.

Estrogens act through binding to nuclear receptors in estrogen-responsive tissues. To date, two estrogen receptors have been identified. These vary in proportion from tissue to tissue.

Circulating estrogens modulate the pituitary secretion of the gonadotropins, luteinizing hormone (LH) and FSH, through a negative feedback mechanism. Estrogens act to reduce the elevated levels of these hormones seen in postmenopausal women.

12.2 Pharmacodynamics

Generally, a serum estrogen concentration does not predict an individual woman’s therapeutic response to Evamist nor her risk for adverse outcomes. Likewise, exposure comparisons across different estrogen products to infer efficacy or safety for the individual woman may not be valid.

12.3 Pharmacokinetics

Absorption

In a multiple-dose study, 72 postmenopausal women were treated for 14 days with Evamist to the inner forearm. Serum concentrations of estradiol appeared to reach steady state after 7 to 8 days of application of one, two, or three 90 mcL sprays of Evamist per day (Figure 1).

Figure 1. Mean (±SD) Serum Estradiol Concentrations on Day 14 Following Topical Application for 14 Days of One, Two or Three Sprays of Evamist (Unadjusted for Baseline)

Pharmacokinetics parameters for estradiol from one, two, or three 90 mcL sprays of Evamist, as assessed on Day 14 of this study, are described in Table 2.

Table 2. Estradiol Pharmacokinetic Parameters on Day 14 (Unadjusted for Baseline)

PK Parameter | Number of Daily Sprays of Evamist
PK Parameter | 1 Spray; (N = 24) | 2 Sprays; (N = 23) | 3 Sprays; (N = 24)
Cmax (pg/mL)a; Cmin (pg/mL)a; Cavg (pg/mL)a; AUC0-24 (pg*hr/mL)a; Tmax (hours)b | 36.4 (62); 11.3 (52); 19.6 (49); 471 (49); 20 (0-24) | 57.4 (94); 18.1 (51); 30.7 (43); 736 (43); 18 (0-24) | 54.1 (50); 19.6 (27); 30.9 (30); 742 (30); 20 (0-24)

aValues expressed are arithmetic means (%CV)

bValues expressed are medians (minimum-maximum)

Distribution

The distribution of exogenous estrogens is similar to that of endogenous estrogens. Estrogens are widely distributed in the body and are generally found in higher concentrations in the sex hormone target organs. Estrogens circulate in blood largely bound to SHBG and albumin.

Metabolism

Exogenous estrogens are metabolized in the same manner as endogenous estrogens. Circulating estrogens exist in a dynamic equilibrium of metabolic interconversions. These transformations take place mainly in the liver. Estradiol is converted reversibly to estrone, and both can be converted to estriol, which is a major urinary metabolite. Estrogens also undergo enterohepatic recirculation via sulfate and glucuronide conjugation in the liver, biliary secretion of conjugates into the intestine, and hydrolysis in the intestine followed by reabsorption. In postmenopausal women, a significant proportion of the circulating estrogens exist as sulfate conjugates, especially estrone sulfate, which serves as a circulating reservoir for the formation of more active estrogens.

Excretion

Estradiol, estrone and estriol are excreted in the urine along with glucuronide and sulfate conjugates.

Potential for Estradiol Transfer

The effect of estradiol transfer was evaluated in 20 healthy postmenopausal women who applied three 90-mcL sprays of Evamist to the inner forearm once daily. One hour after applying Evamist, subjects held the dosed forearm against the inner forearm of a non-dosed (recipient) male subject for one 5-minute period of continual contact. A 4% increase in serum estradiol exposure was observed in persons who came in contact with the application site. The possibility of unintentional secondary exposure to Evamist should be brought to the attention of physicians and Evamist users.

Effect of Application Site Washing

Site washing with warm water and soap one hour after the application of three 90 mcL sprays to the inner forearm did not have a significant effect on average 24-hour serum concentrations of estradiol.

13 NONCLINICAL TOXICOLOGY

13.1 Carcinogenesis, Mutagenesis, Impairment of Fertility

Long-term continuous administration of natural and synthetic estrogens in certain animal species increases the frequency of carcinomas of the breast, uterus, cervix, vagina, testis and liver.

14 CLINICAL STUDIES

14.1 Effects on Vasomotor Symptoms in Postmenopausal Women

In a 12-week, randomized, double-blind, placebo-controlled clinical trial, a total of 454 postmenopausal women (average 53 years of age, 70 percent Caucasian and 24 percent African-American) were randomized and received at least one dose of Evamist (one, two or three 90 mcL sprays) or placebo. Generally healthy postmenopausal women were enrolled with a mean total frequency of ≥56 moderate to severe vasomotor symptoms per week (≥8 per day).

Efficacy was determined as a statistically significant and clinically significant (at least two per day or 14 per week difference) reduction in hot flush frequency and a statistically significant reduction in severity for Evamist versus placebo. One, two or three daily sprays of Evamist were shown to be better than placebo for relief of frequency (Table 3) and severity (Table 4) of moderate to severe vasomotor symptoms at Week 4 and Week 12.

Table 3. Effect of Treatment on the Daily Frequency of Moderate to Severe Vasomotor Symptoms at Week 4 and Week 12 (Intent-To-Treat Population, LOCF)

 |  | Mean Change from Baselinea (SD)
Treatment; (N) | Baseline; Mean (SD) | Week 4; Mean (SD) | Week 12; Mean (SD)
1 Spray
Evamist (N=76) | 11.81 (4.07) | -6.26 (4.01) | -8.10 (4.02)
Placebo (N=77) | 12.41 (5.59) | -3.64 (5.30) | -4.76 (5.84)
Differenceb | — | -2.62 | -3.34
p-valuec | — | 0.0010 | 0.0004
2 Sprays
Evamist (N=74) | 12.66 (7.33) | -7.30 (6.93) | -8.66 (6.65)
Placebo (N=76) | 12.13 (6.10) | -4.74 (4.38) | -6.19 (5.77)
Differenceb | — | -2.56 | -2.47
p-valuec | — | 0.0027 | 0.0099
3 Sprays
Evamist (N=76) | 10.78 (3.58) | -6.64 (4.23) | -8.44 (4.50)
Placebo (N=75) | 12.55 (11.94) | -4.54 (7.40) | -5.32 (6.30)
Differenceb | — | -2.10 | -3.12
p-valuec | — | 0.0002 | <0.0001

aMean change and difference based on raw data

bEvamist versus placebo

cTests for pairwise differences using ANCOVA

Table 4. Effect of Treatment on the Weekly Severity of Moderate to Severe Vasomotor Symptoms at Week 4 and Week 12 (Intent-To-Treat Population, LOCF)a

 |  | Mean Change from Baselineb (SD)
Treatment; (N) | Baseline; Mean (SD) | Week 4; Mean (SD) | Week 12; Mean (SD)
1 Spray
Evamist (N=76) | 2.53 (0.25) | -0.47 (0.80) | -1.04 (1.01)
Placebo (N=77) | 2.55 (0.25) | -0.19 (0.55) | -0.26 (0.60)
Differencec | — | -0.28 | -0.78
p-valued | — | 0.0573 | <0.0001
2 Sprays
Evamist (N=74) | 2.54 (0.21) | -0.57 (0.83) | -0.92 (1.01)
Placebo (N=76) | 2.54 (0.22) | -0.25 (0.64) | -0.54 (0.89)
Differencec | — | -0.32 | -0.38
p-valued | — | 0.0160 | 0.0406
3 Sprays
Evamist (N=76) | 2.58 (0.25) | -0.43 (0.66) | -1.07 (1.01)
Placebo (N=75) | 2.54 (0.24) | -0.13 (0.53) | -0.31 (0.75)
Differencec | — | -0.30 | -0.76
p-valued | — | 0.0031 | <0.0001

aSeverity score calculated as: (2 x number moderate + 3 x number severe) / (number moderate + number severe)

bMean change and difference based on raw data

cEvamist versus placebo

dTests for pairwise differences using ANCOVA

14.2 Women’s Health Initiative Studies

The WHI enrolled approximately 27,000 predominantly healthy postmenopausal women in two substudies to assess the risks and benefits of daily oral CE (0.625 mg)-alone or in combination with MPA (2.5 mg) compared to placebo in the prevention of certain chronic diseases. The primary endpoint was the incidence of CHD (defined as nonfatal MI, silent MI and CHD death), with invasive breast cancer as the primary adverse outcome. A “global index” included the earliest occurrence of CHD, invasive breast cancer, stroke, PE, endometrial cancer (only in the CE plus MPA substudy), colorectal cancer, hip fracture, or death due to other cause. These substudies did not evaluate the effects of CE-alone or CE plus MPA on menopausal symptoms.

WHI Estrogen-Alone Substudy

The WHI estrogen-alone substudy was stopped early because an increased risk of stroke was observed, and it was deemed that no further information would be obtained regarding the risks and benefits of estrogen-alone in predetermined primary endpoints. Results of the estrogen alone substudy, which included 10,739 women (average 63 years of age, range 50 to 79 years of age; 75.3 percent White, 15.1 percent Black, 6.1 percent Hispanic, 3.6 percent Other), after an average follow-up of 7.1 years are presented in Table 5.

Table 5. Relative and Absolute Risk Seen in the Estrogen Alone Substudy of WHIa

Event | Relative Risk; CE vs. Placebo; (95% nCIb) | CE; (n = 5,310) | Placebo; (n = 5,429)
Event | Relative Risk; CE vs. Placebo; (95% nCIb) | Absolute Risk per; 10,000 Women-Years
CHD eventsc; Non-fatal MIc CHD death c; CHD death c | 0.95 (0.78-1.16); 0.91 (0.73-1.14); 1.01 (0.71-1.43) | 54; 40; 16 | 57; 43; 16
All strokesc; Ischemic stroke c | 1.33 (1.05-1.68); 1.55 (1.19-2.01) | 45; 38 | 33; 25
Deep vein thrombosisc,d | 1.47 (1.06-2.06) | 23 | 15
Pulmonary embolismc | 1.37 (0.90-2.07) | 14 | 10
Invasive breast cancerc | 0.80 (0.62-1.04) | 28 | 34
Colorectal cancere | 1.08 (0.75-1.55) | 17 | 16
Hip fracturec | 0.65 (0.45-0.94) | 12 | 19
Vertebral fracturesc,d | 0.64 (0.44-0.93) | 11 | 18
Lower arm/wrist fracturesc,d | 0.58 (0.47-0.72) | 35 | 59
Total fracturesc,d | 0.71 (0.64-0.80) | 144 | 197
Death due to other causese,f | 1.08 (0.88-1.32) | 53 | 50
Overall mortalityc,d | 1.04 (0.88-1.22) | 79 | 75
Global indexg | 1.02 (0.92-1.13) | 206 | 201

aAdapted from numerous WHI publications. WHI publications can be viewed at www.nhlbi.nih.gov/whi.

bNominal confidence intervals unadjusted for multiple looks and multiple comparisons.

cResults are based on centrally adjudicated data for an average follow-up of 7.1 years.

dNot included in “global index”.

eResults are based on an average follow-up of 6.8 years.

fAll deaths, except from breast or colorectal cancer, definite or probable CHD, PE or cerebrovascular disease.

gA subset of the events was combined in a “global index”, defined as the earliest occurrence of CHD events, invasive breast cancer, stroke, PE, endometrial cancer, colorectal cancer, hip fracture, or death due to other causes.

For those outcomes included in the WHI “global index” that reached statistical significance, the absolute excess risk per 10,000 women-years in the group treated with CE-alone was 12 more strokes, while the absolute risk reduction per 10,000 women-years was 7 fewer hip fractures.^9 The absolute excess risk of events included in the “global index” was a non-significant 5 events per 10,000 women-years. There was no difference between the groups in terms of all-cause mortality.

No overall difference for primary CHD events (nonfatal MI, silent MI and CHD death) and invasive breast cancer incidence in women receiving CE-alone compared to placebo was reported in final centrally adjudicated results from the estrogen-alone substudy, after an average follow-up of 7.1 years.

Centrally adjudicated results for stroke events from the estrogen-alone substudy, after an average follow-up of 7.1 years, reported no significant differences in distribution of stroke subtypes or severity, including fatal strokes, in women receiving CE-alone compared to placebo. Estrogen-alone increased the risk for ischemic stroke, and this excess risk was present in all subgroups of women examined.^10

Timing of the initiation of estrogen-alone therapy relative to the start of menopause may affect the overall risk benefit profile. The WHI estrogen-alone substudy stratified by age showed in women 50 to 59 years of age a non-significant trend toward reduced risk for CHD [hazard ratio (HR) 0.63 (95 percent CI, 0.36-1.09)] and overall mortality [HR 0.71 (95 percent CI, 0.46-1.11)].

WHI Estrogen Plus Progestin Substudy

The WHI estrogen plus progestin substudy was stopped early. According to the predefined stopping rule, after an average follow-up of 5.6 years of treatment, the increased risk of invasive breast cancer and cardiovascular events exceeded the specified benefits included in the “global index”. The absolute excess risk of events included in the “global index” was 19 per 10,000 women-years.

For those outcomes included in the WHI “global index” that reached statistical significance after 5.6 years of follow-up, the absolute excess risks per 10,000 women-years in the group treated with CE plus MPA were 7 more CHD events, 8 more strokes, 10 more PEs, and 8 more invasive breast cancers, while the absolute risk reduction per 10,000 women-years were 6 fewer colorectal cancers and 5 fewer hip fractures.

Results of the CE plus MPA substudy which included 16,608 women (average 63 years of age; range 50 to 79 years of age: 83.9 percent White, 6.5 percent Black, 5.4 percent Hispanic, 3.9 percent Other) are presented in Table 6. These results reflect centrally adjudicated data after an average follow-up of 5.6 years.

Table 6. Relative and Absolute Risk Seen in the Estrogen Plus Progestin Substudy of WHI at an Average of 5.6 Yearsa,b

Event | Relative Risk; CE/MPA vs. Placebo; (95% nCIc) | CE/MPA; (n = 8,506) | Placebo; (n = 8,102)
Event | Relative Risk; CE/MPA vs. Placebo; (95% nCIc) | Absolute Risk per; 10,000 Women-Years
CHD events; Non-fatal MI CHD death c; CHD death c | 1.23 (0.99-1.53); 1.28 (1.00-1.63); 1.10 (0.70-1.75) | 41; 31; 8 | 34; 25; 8
All strokes; Ischemic stroke | 1.31 (1.03-1.68); 1.44 (1.09-1.90) | 33; 26 | 25; 18
Deep vein thrombosisd | 1.95 (1.43-2.67) | 26 | 13
Pulmonary embolism | 2.13 (1.45-3.11) | 18 | 8
Invasive breast cancere | 1.24 (1.01-1.54) | 41 | 33
Colorectal cancer | 0.61 (0.42-0.87) | 10 | 16
Endometrial cancerd | 0.81 (0.48-1.36) | 6 | 7
Cervical cancerd | 1.44 (0.47-4.42) | 2 | 1
Hip fracture | 0.67 (0.47-0.96) | 11 | 16
Vertebral fracturesd | 0.65 (0.46-0.92) | 11 | 17
Lower arm/wrist fracturesd | 0.71 (0.59-0.85) | 44 | 62
Total fracturesd | 0.76 (0.69-0.83) | 152 | 199
Overall mortalityf | 1.00 (0.83-1.19) | 52 | 52
Global indexg | 1.13 (1.02-1.25) | 184 | 165

aAdapted from numerous WHI publications, WHI publications can be viewed at www.nhlbi.nih.gov/whi.

bResults are based on centrally adjudicated data.

cNominal confidence intervals unadjusted for multiple looks and multiple comparisons.

dNot included in “global index”.

eIncludes metastatic and non-metastatic breast cancer, with the exception of in situ breast cancer.

fAll deaths, except from breast or colorectal cancer, definite or probable CHD, PE or cerebrovascular disease.

gA subset of the events was combined in a “global index”, defined as the earliest occurrence of CHD events, invasive breast cancer, stroke, PE, endometrial cancer, colorectal cancer, hip fracture, or death due to other causes.

Timing of the initiation of estrogen plus progestin therapy relative to the start of menopause may affect the overall risk benefit profile. The WHI estrogen plus progestin substudy stratified by age showed in women 50 to 59 years of age a non-significant trend toward reduced risk for overall mortality [HR 0.69 (95 percent CI, 0.44-1.07)].

14.3 Women’s Health Initiative Memory Study

The WHIMS estrogen-alone ancillary study of the WHI, enrolled 2,947 predominantly healthy hysterectomized postmenopausal women 65 to 79 years of age and older (45 percent were 65 to 69 years of age, 36 percent were 70 to 74 years of age, and 19 percent were 75 years of age and older) to evaluate the effects of daily CE (0.625 mg) on the incidence of probable dementia (primary outcome) compared to placebo.

After an average follow-up of 5.2 years, the relative risk of probable dementia for CE-alone versus placebo was 1.49 (95 percent CI, 0.83-2.66). The absolute risk of probable dementia for CE-alone versus placebo was 37 versus 25 cases per 10,000 women-years. Probable dementia as defined in this study included Alzheimer’s disease (AD), vascular dementia (VaD) and mixed type (having features of both AD and VaD). The most common classification of probable dementia in the treatment group and the placebo group was AD. Since the ancillary study was conducted in women 65 to 79 years of age, it is unknown whether these findings apply to younger postmenopausal women [see Warnings and Precautions (5.3) and Use in Specific Populations (8.5)].

The WHIMS estrogen plus progestin ancillary study of WHI enrolled 4,532 predominantly healthy postmenopausal women 65 years of age and older (47 percent were 65 to 69 years of age, 35 percent were 70 to 74 years of age, and 18 percent were 75 years of age and older) to evaluate the effects of daily CE (0.625 mg) plus MPA (2.5 mg) on the incidence of probable dementia (primary outcome) compared to placebo.

After an average follow-up of 4 years, the relative risk of probable dementia for CE plus MPA versus placebo was 2.05 (95 percent CI, 1.12-3.48). The absolute risk of probable dementia for CE plus MPA versus placebo was 45 versus 22 per 10,000 women-years. Probable dementia as defined in this study included AD, VaD and mixed type (having features of both AD and VaD). The most common classification of probable dementia in the treatment group and the placebo group was AD. Since the ancillary study was conducted in women 65 to 79 years of age, it is unknown whether these findings apply to younger postmenopausal women [see Warnings and Precautions (5.3) and Use in Specific Populations (8.5)].

When data from the two populations were pooled as planned in the WHIMS protocol, the reported overall relative risk for probable dementia was 1.76 (95 percent CI, 1.19-2.60). Differences between groups became apparent in the first year of treatment. It is unknown whether these findings apply to younger postmenopausal women [see Warnings and Precautions (5.3) and Use in Specific Populations (8.5)].

15 REFERENCES

1. Rossouw JE, et al. Postmenopausal Hormone Therapy and Risk of Cardiovascular Disease by Age and Years Since Menopause. JAMA. 2007:297;1465-1477.
2. Hsia J, et al. Conjugated Equine Estrogens and Coronary Heart Disease. Arch Int Med. 2006;166:357–365.
3. Curb JD, et al. Venous Thrombosis and Conjugated Equine Estrogen in Women Without a Uterus. Arch Int Med. 2006;166:772-780.
4. Cushman M, et al. Estrogen Plus Progestin and Risk of Venous Thrombosis. JAMA. 2004:292;1573-1580.
5. Stefanick ML, et al. Effects of Conjugated Equine Estrogens on Breast Cancer and Mammography Screening in Postmenopausal Women with Hysterectomy. JAMA. 2006;295:1647-1657.
6. Chlebowski RT, et al. Influence of Estrogen Plus Progestin on Breast Cancer and Mammography in Healthy Postmenopausal Women. JAMA. 2003:289;3234-3253.
7. Anderson GL, et al. Effects of Estrogen Plus Progestin in Gynecologic Cancers and Associated Diagnostic Procedures. JAMA. 2003:290;1739-1748.
8. Shumaker SA, et al. Conjugated Equine Estrogens and Incidence of Probable Dementia and Mild Cognitive Impairment in Postmenopausal Women. JAMA. 2004:291;2947-2958.
9. Jackson RD, et al. Effects of Conjugated Equine Estrogen on Risk of Fractures and BMD in Postmenopausal Women with Hysterectomy: Results from the Women’s Health Initiative Randomized Trial. J Bone Miner Res. 2006:21;817-828.
10. Hendrix SL, et al. Effects of Conjugated Equine Estrogen on Stroke in the Women’s Health Initiative. Circulation. 2006:113;2425-2434.

16 HOW SUPPLIED/STORAGE AND HANDLING

16.1 How Supplied

Evamist (NDC 0574-2067-27) is supplied as a homogeneous solution of estradiol USP, octisalate USP and alcohol USP. The liquid formulation of Evamist is packaged in a glass vial fitted with a metered-dose pump. The unit is encased in a plastic housing with a conical bell opening that controls the distance, angle, and area of application of the metered-dose spray. Each metered-dose pump contains 8.1 mL and is designed to deliver 56 sprays of 90 mcL after priming. One spray contains 1.53 mg estradiol.

16.2 Storage and Handling

Keep out of reach of children.

Alcohol and alcohol-based liquids are flammable. Avoid fire, flame or smoking until the spray has dried.

Store at room temperature 20°C to 25°C (68°F to 77°F); excursion permitted between 15°C to 30°C (59°F to 86°F). Do not freeze.

17 PATIENT COUNSELING INFORMATION

Advise women to read the FDA-approved patient labeling (Patient Information and Instructions for Use).

Vaginal Bleeding

Inform postmenopausal women to report any vaginal bleeding to their healthcare provider as soon as possible [see Warnings and Precautions (5.2)].

Unintentional Secondary Exposure to Evamist

Provide the following information about secondary exposure to Evamist:

- Apply Evamist as directed and keep children from contacting exposed application site(s). If direct contact with the application site occurs, the contact area should be washed thoroughly with soap and water. Women should cover the Evamist application site, after the 2 minute drying period, with clothing if another person may come in contact with that area of skin. [See FDA-Approved Patient Information Leaflet at the end of the prescribing information.]
- Look for signs of unexpected sexual development, such as breast mass or increased breast size in prepubertal children.
- If signs of unintentional secondary exposure are noticed:
- Have children evaluated by a healthcare provider.
- Discontinue Evamist until the cause(s) is identified for any unexpected sexual development in children under their care.
- Women should contact their healthcare provider and discuss the appropriate use and handling of Evamist when around children.
- If conditions for safe use cannot be met, Evamist should be discontinued and alternative treatments for menopausal signs and symptoms should be considered.
- Pets may also be unintentionally exposed to Evamist if above precautions are not followed.

Possible Serious Adverse Reactions with Estrogen-Alone Therapy

Inform postmenopausal women of the possible serious adverse reactions of estrogen-alone therapy including Cardiovascular Disorders, Malignant Neoplasms, and Probable Dementia [see Warnings and Precautions (5.1, 5.2, 5.3)].

Possible Common Adverse Reactions with Estrogen-Alone Therapy

Inform postmenopausal women of possible less serious but common adverse reactions of estrogen-alone therapy such as headache, breast pain and tenderness, nausea and vomiting.

Manufactured by Padagis®

Yeruham, Israel

www.padagis.com

Rev 10-2024

9E400 RC PH3

Patient Information

EVAMIST (EE-vuh-mist)

(estradiol transdermal spray)

Read this Patient Information before you start using EVAMIST and each time you get a refill. There may be new information. This information does not take the place of talking to your healthcare provider about your menopausal symptoms or your treatment.

What is the most important information I should know about EVAMIST (an estrogen hormone)?

• Using estrogen-alone may increase your chance of getting cancer of the uterus (womb).

• Report any unusual vaginal bleeding right away while you are using EVAMIST. Vaginal bleeding after menopause may be a warning sign of cancer of the uterus (womb). Your healthcare provider should check any unusual vaginal bleeding to find out the cause.

• Do not use estrogen-alone to prevent heart disease, heart attacks, strokes or dementia (decline in brain function).

• Using estrogen-alone may increase your chances of getting strokes or blood clots.

• Using estrogen-alone may increase your chance of getting dementia, based on a study of women 65 years and older.

• Do not use estrogens with progestogens to prevent heart disease, heart attack, strokes, or dementia.

• Using estrogens with progestogens may increase your chances of getting heart attacks, strokes, breast cancer, or blood clots.

• Using estrogens with progestogens may increase your chance of getting dementia, based on a study of women 65 years and older.

• The estrogen in EVAMIST spray can transfer from the area of skin where it was sprayed to other people. Do not allow others, especially children, to come into contact with the area of your skin where you sprayed EVAMIST. Young children who are accidentally exposed to estrogen through contact with women using EVAMIST may show signs of puberty that are not expected (for example, breast budding).

• Only one estrogen-alone product and dose have been shown to increase your chances of getting strokes, blood clots, and dementia. Only one estrogen with progestogen product and dose have been shown to increase your chances of getting heart attacks, strokes, breast cancer, blood clots, and dementia. Because other products and doses have not been studied in the same way, it is not known how the use of EVAMIST will affect your chances of these conditions. You and your healthcare provider should talk regularly about whether you still need treatment with EVAMIST.

What is EVAMIST?

EVAMIST is a prescription medicine spray that contains estradiol (an estrogen hormone).

What is EVAMIST used for?

EVAMIST spray is used after menopause to:

- Reduce moderate to severe hot flashes
Estrogens are hormones made by a woman's ovaries. The ovaries normally stop making estrogens when a woman is between 45 and 55 years old. This drop in body estrogen levels causes the “change of life” or menopause (the end of monthly menstrual periods). Sometimes, both ovaries are removed during an operation before natural menopause takes place. The sudden drop in estrogen levels causes “surgical menopause.”
When the estrogen levels begin dropping, some women get very uncomfortable symptoms, such as feelings of warmth in the face, neck, and chest, or sudden intense feelings of heat and sweating (“hot flashes” or “hot flushes”). In some women, the symptoms are mild, and they will not need to use estrogens. In other women, symptoms can be more severe. You and your healthcare provider should talk regularly about whether you still need treatment with EVAMIST.

Who should not use EVAMIST?

Do not start using EVAMIST if you:

- have unusual vaginal bleeding.
Vaginal bleeding after menopause may be a warning sign of cancer of the uterus (womb). Your healthcare provider should check any unusual vaginal bleeding to find out the cause.
- have been diagnosed with a bleeding disorder.
- currently have or have had certain cancers.
Estrogens may increase the chance of getting certain types of cancers, including cancer of the breast or uterus (womb). If you have or have had cancer, talk with your healthcare provider about whether you should use EVAMIST.
- had a stroke or heart attack.
- currently have or have had blood clots.
- currently have or have had liver problems.
- are allergic to EVAMIST or any of its ingredients.

See the list of ingredients in EVAMIST at the end of this leaflet

Before you use EVAMIST, tell your healthcare provider about all of your medical conditions, including if you:

- have any unusual vaginal bleeding.
Vaginal bleeding after menopause may be a warning sign of cancer of the uterus (womb). Your healthcare provider should check any vaginal bleeding to find out the cause.
- have any other medical conditions that may become worse while you are using EVAMIST.
Your healthcare provider may need to check you more carefully if you have certain conditions, such as asthma (wheezing), epilepsy (seizures), diabetes, migraine, endometriosis, lupus, angioedema (swelling of face or tongue), or problems with your heart, liver, thyroid, kidneys, or have high calcium levels in your blood.
- are going to have surgery or will be on bed rest.
Your healthcare provider will let you know if you need to stop using EVAMIST.
- are pregnant or think you may be pregnant.
EVAMIST is not for pregnant women.
- are breastfeeding.
The hormone in EVAMIST can pass into your breast milk.

Tell your healthcare provider about all the medicines you take including prescription and over-the-counter medicines, vitamins and herbal supplements. Some medicines may affect how EVAMIST works. Some other medicines and food products may increase or decrease the concentration of the hormone in EVAMIST in the blood. EVAMIST may affect how your other medicines work, and other medicines may affect how EVAMIST works. Keep a list of your medicines and show it to your healthcare provider and pharmacist when you get a new medicine.

How should I use EVAMIST?

For detailed instructions, see the step-by-step instructions for using EVAMIST at the end of this Patient Information.

- Use EVAMIST exactly as your healthcare provider tells you to use it.
- EVAMIST is for skin use only.
- Apply EVAMIST at the same time each day.
- If you use sunscreen 1 hour after you use EVAMIST, it may reduce the amount of EVAMIST absorbed by your skin.
- The estrogen in EVAMIST spray can transfer from the area of skin where it was sprayed to other people or pets. Do not allow other people, especially children to come into contact with the area of your skin where you have sprayed EVAMIST.
- If another person accidentally touches the area of your skin where you have sprayed EVAMIST, that area of their skin should be washed with soap and water right away.
- Do not let pets lick or touch your arm where you have sprayed EVAMIST, especially small pets. EVAMIST may harm them. Cover your skin with clothing where you have sprayed EVAMIST if you think a pet could come in contact with that area of your skin.
- If a pet accidentally comes in contact with the area of your skin where you have sprayed EVAMIST, the area of the pet’s skin should be washed with soap and water right away.
- Young children who are accidentally exposed to estrogen through contact with women using EVAMIST may show signs and symptoms of puberty that are not expected. Signs and symptoms in children of exposure to EVAMIST may include:
- breast budding or breast lumps
- other signs of abnormal sexual development
If a child shows signs and symptoms of accidental exposure to EVAMIST:
  1. have the child checked right away by their healthcare provider.
  2. stop using EVAMIST and call your healthcare provider right away.
  3. talk to your healthcare provider about the correct use of EVAMIST when around children.
- Talk to your healthcare provider about other treatments for your menopause symptoms if accidental exposure to EVAMIST cannot be avoided.
- You and your healthcare provider should talk regularly (for example, every 3 to 6 months) about the dose you are taking and whether you still need treatment with EVAMIST.

What should I avoid while using EVAMIST?

- Do not allow others to make contact with the area of skin where you have applied the EVAMIST spray.
- EVAMIST contains alcohol, which is flammable. Avoid fire, flame, or smoking until the area of your skin where you have applied EVAMIST has dried.

What are the possible side effects of EVAMIST?

Side effects are grouped by how serious they are and how often they happen when you are treated.

Serious, but less common side effects include:

- heart attack
- stroke
- blood clots
- breast cancer
- cancer of the lining of the uterus (womb)
- cancer of the ovary
- dementia
- gallbladder disease
- high or low calcium levels
- changes in vision
- high blood pressure
- high levels of fat in your blood (triglycerides)
- liver problems
- changes in thyroid hormone levels
- swelling or fluid retention
- cancer changes of endometriosis
- enlargement of benign tumors of the uterus (“fibroids”)
- worsening swelling of face or tongue (angioedema) in women who have a history of angioedema
- changes in laboratory test results such as bleeding time and high blood sugar levels

Call your healthcare provider right away if you get any of the following warning signs or any other unusual symptoms that concern you:

- new breast lumps
- unusual vaginal bleeding
- changes in vision or speech
- sudden new severe headaches
- severe pains in your chest or legs with or without shortness of breath, weakness and fatigue

Common side effects of EVAMIST include:

- headache
- breast pain
- irregular vaginal bleeding or spotting
- stomach or abdominal cramps, bloating
- nausea and vomiting
- hair loss
- fluid retention
- vaginal yeast infection

Tell your healthcare provider if you have any side effects that bother you or do not go away. These are not all the possible side effects of EVAMIST. Call your doctor for medical advice about side effects. You may also report side effects to Padagis® at 1-866-634-9120 or to FDA at 1-800-FDA-1088.

What can I do to lower my chances of a serious side effect with EVAMIST?

- Talk with your healthcare provider regularly about whether you should continue using EVAMIST.
- If you have a uterus, talk with your healthcare provider about whether the addition of a progestogen is right for you.
- In general, the addition of a progestogen is recommended for women with a uterus to reduce the chance of getting cancer of the uterus (womb).
- See your healthcare provider right away if you get vaginal bleeding while using EVAMIST.
- Have a pelvic exam, breast exam, and mammogram (breast X-ray) every year unless your healthcare provider tells you something else.
- If members of your family have had breast cancer or if you have ever had breast lumps or an abnormal mammogram, you may need to have breast exams more often.
- If you have high blood pressure, high cholesterol (fat in the blood), diabetes, are overweight, or if you use tobacco, you may have a higher chance of getting heart disease.

Ask your healthcare provider for ways to lower your chances of getting heart disease.

How should I store EVAMIST?

- Store EVAMIST at room temperature 68°F to 77°F (20°C to 25°C)
- Do not freeze.
- Safely throw away medicine that is out of date or no longer needed.

Keep EVAMIST and all medicines out of the reach of children.

General information about the safe and effective use of EVAMIST.

Medicines are sometimes prescribed for purposes other than those listed in Patient Information leaflets. Do not use EVAMIST for a condition for which it was not prescribed. Do not give EVAMIST to other people, even if they have the same symptoms you have. It may harm them.

You can ask your pharmacist or healthcare provider for information about EVAMIST that is written for health professionals.

For more information, go to www.Evamist.com or call Padagis® at 1-866-634-9120.

What are the ingredients in EVAMIST?

Active ingredient: estradiol

Inactive ingredients: octisalate, alcohol

Instructions for Use

EVAMIST (EE-vuh-mist)

(estradiol transdermal spray)

Read this Instructions for Use before you start using EVAMIST and each time you get a refill. There may be new information. This information does not take the place of talking to your healthcare provider about your menopausal symptoms or your treatment.

The parts of your EVAMIST applicator

EVAMIST comes in a spray applicator that delivers a measured amount of estradiol to your skin with each spray (see Figure A).

Step 1. Priming your EVAMIST

- Before you use your EVAMIST applicator for the first time, the applicator must be primed.
- Hold the EVAMIST applicator upright. Keep the cover on. Fully press down the pump button 5 times with your thumb or index finger (see Figure B). After priming, the EVAMIST applicator is ready to use.
- The EVAMIST applicator should be primed only 1 time when you first start using a new applicator. Do not prime the EVAMIST applicator before your dose each day.

Step 2. Using your EVAMIST

- Remove the plastic cover.
- Apply EVAMIST to a clean, dry, unbroken skin area on the inside of your forearm between the elbow and the wrist (see Figure C). This area must be clean, dry, and the skin must be without open wounds, cuts, abrasions, or rashes.
- Hold the EVAMIST applicator upright and rest the plastic cone flat against your skin. You may need to change the position of your arm or the position of the cone on your arm so that the cone is flat against your skin and there are no gaps between the cone and your skin (see Figure C).
- Press the pump button down fully 1 time (see Figure C).

If your healthcare provider tells you to increase your dose to 2 or 3 sprays, move the cone before applying the second or third spray to an area of your skin next to but not touching the area of the previous spray (see Figure D).

- Do not apply EVAMIST to your breasts or in and around your vagina.
- Do not massage or rub EVAMIST into your skin.
- Let EVAMIST spray dry on your skin for at least:
- 2 minutes before you cover your skin with clothing.
- 1 hour before you wash your skin.

Step 3. After you use EVAMIST

- Place the plastic cover back on the EVAMIST applicator cone.
- EVAMIST is flammable until dry. Avoid fire, flame, or smoking until the area of your skin where you have applied EVAMIST has completely dried.

Step 4. Throwing away used EVAMIST applicators

- Your EVAMIST applicator contains enough medicine to allow for initial priming of the pump with 5 sprays and application of 56 sprays.
- Do not use your EVAMIST applicator for more than 56 application sprays even though the bottle may not be completely empty. You may not get the correct dose.
- Always replace the cover over the cone of your EVAMIST applicator before you throw it away to prevent accidental exposure to other people or pets.

This Patient Information and Instructions for Use have been approved by the U.S. Food and Drug Administration.

Manufactured by Padagis®

Yeruham, Israel

www.padagis.com

Rev 10-2024
9E400 RC PH3

PACKAGE/LABEL PRINCIPAL DISPLAY PANEL

FOR TOPICAL USE ONLY

NDC 0574-2067-27

Evamist®

(estradiol transdermal spray)

Each spray contains 1.53 mg of estradiol

0.27 fl oz (8.1 mL)

Rx Only